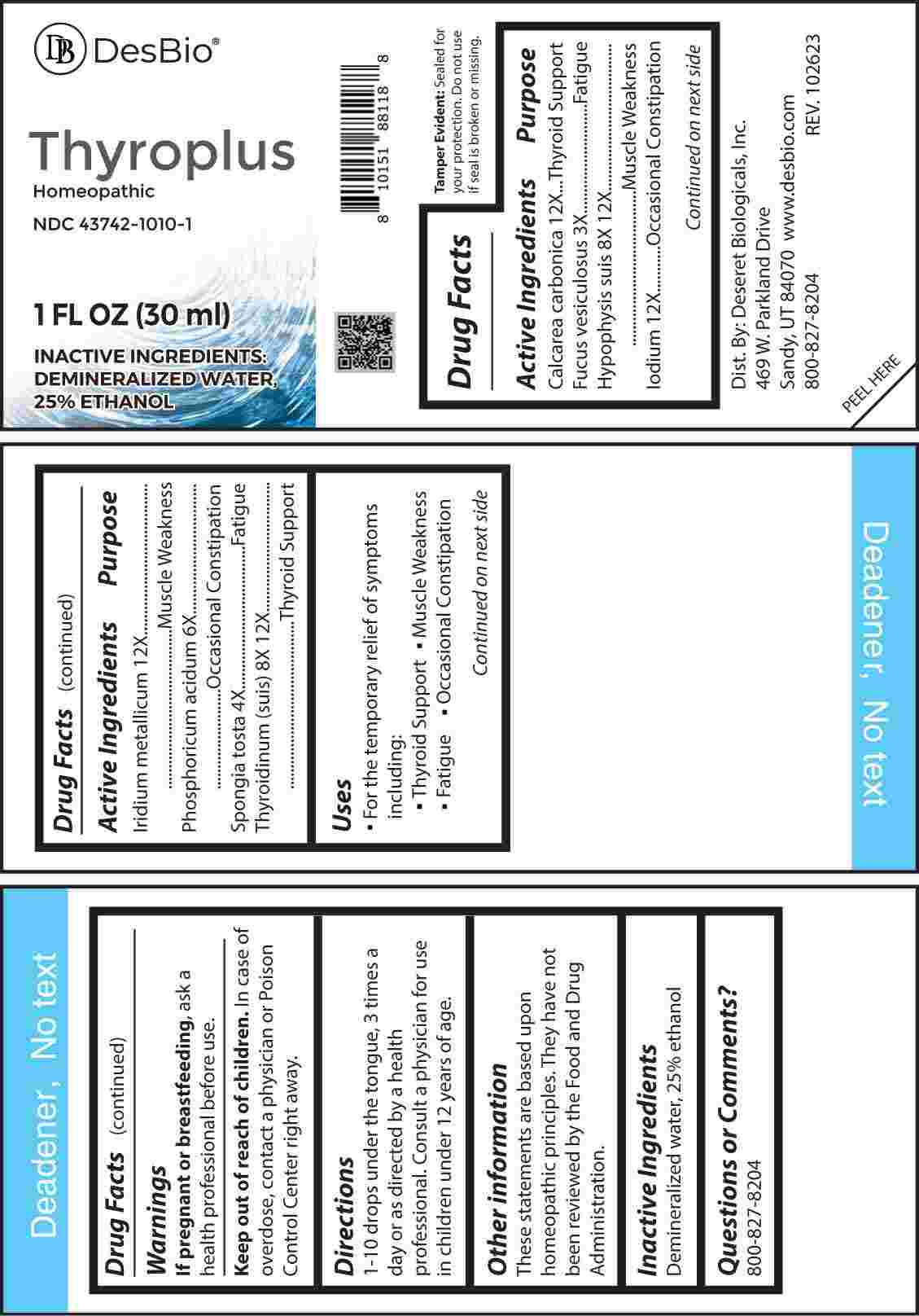 DRUG LABEL: Thyroplus
NDC: 43742-1010 | Form: LIQUID
Manufacturer: Deseret Biologicals, Inc.
Category: homeopathic | Type: HUMAN OTC DRUG LABEL
Date: 20240306

ACTIVE INGREDIENTS: FUCUS VESICULOSUS 3 [hp_X]/1 mL; SPONGIA OFFICINALIS SKELETON, ROASTED 4 [hp_X]/1 mL; PHOSPHORIC ACID 6 [hp_X]/1 mL; SUS SCROFA PITUITARY GLAND 8 [hp_X]/1 mL; THYROID 8 [hp_X]/1 mL; OYSTER SHELL CALCIUM CARBONATE, CRUDE 12 [hp_X]/1 mL; IODINE 12 [hp_X]/1 mL; IRIDIUM 12 [hp_X]/1 mL
INACTIVE INGREDIENTS: WATER; ALCOHOL

DRUG FACTS:

ACTIVE INGREDIENTS:

Calcarea Carbonica 12X, Fucus Vesiculosus 3X, Hypophysis Suis 8X, 12X, Iodium 12X, Iridium Metallicum 12X, Phosphoricum Acidum 6X, Spongia Tosta 4X, Thyroidinum 8X, 12X.

PURPOSE:

Calcarea Carbonica – Thyroid Support, Fucus Vesiculosus - Fatigue, Hypophysis Suis – Muscle Weakness, Iodium – Occasional Constipation, Iridium Metallicum – Muscle Weakness, Phosphoricum Acidum – Occasional Constipation, Spongia Tosta - Fatigue, Thyroidinum – Thyroid Support

USES:

• For the temporary relief of symptoms including:

• Thyroid Support • Muscle Weakness

• Fatigue • Occasional Constipation

These statements are based upon homeopathic principles. They have not been reviewed by the Food and Drug Administration.

WARNINGS:

If pregnant or breast-feeding, ask a health professional before use.

Keep out of reach of children. In case of overdose, contact a physician or Poison Control Center right away.

Tamper Evident: Sealed for your protection. Do not use if seal is broken or missing.

KEEP OUT OF REACH OF CHILDREN:

In case of overdose, contact a physician or Poison Control Center right away.

DIRECTIONS:

1-10 drops under the tongue, 3 times a day or as directed by a health professional. Consult a physician for use in children under 12 years of age.

INACTIVE INGREDIENTS:

Demineralized water, 25% ethanol

QUESTIONS:

Dist. By: Deseret Biologicals, Inc.

469 W. Parkland Drive

Sandy, UT 84070

www.desbio.com

800-827-8204

PACKAGED LABEL DISPLAY:

Des Bio

Thyroplus

Homeopathic

NDC 43742-1010-1

1 FL OZ (30 ml)